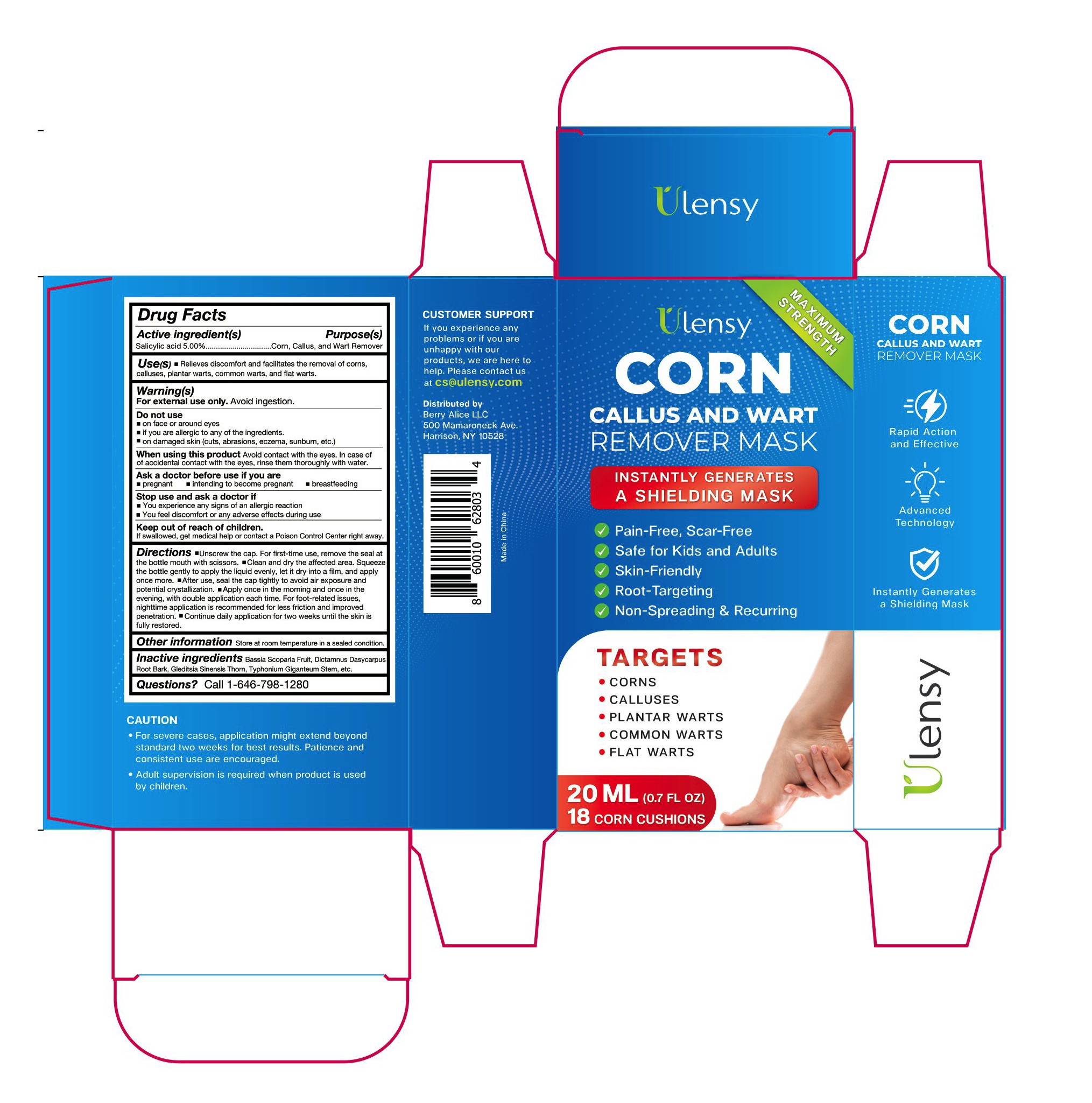 DRUG LABEL: Ulensy Corn Callus and Wart Remover
NDC: 83818-003 | Form: LIQUID
Manufacturer: Shenzhen Xinxin Yunhai Technology Co., Ltd.
Category: otc | Type: HUMAN OTC DRUG LABEL
Date: 20240118

ACTIVE INGREDIENTS: SALICYLIC ACID 5 g/100 mL
INACTIVE INGREDIENTS: BASSIA SCOPARIA FRUIT; DICTAMNUS DASYCARPUS ROOT BARK; GLEDITSIA SINENSIS THORN; TYPHONIUM GIGANTEUM STEM

83818-003

Active Ingredient

Salicylic acid 5%

Purpose

Corn, Callus, and Wart Remover

Use

Relieves discomfort and facilitates the removal of corns, products, we are here to REMOVER MASK calluses, plantar warts, common warts, and flat warts.

Warnings

For external use only. Avoid ingestion.

Do not use

around eyes or on facial area if you have a known allergy to this product on damaged skin

When Using

avoid eye contact. If the product gets into eyes, thoroughly rinse with water.

Stop Use

Avoid contact with the eyes. In case of accidental contact with the eyes, rinse them thoroughly with water.

Ask Doctor

pregnant, intending to become pregnant, breastfeeding

Keep Oot Of Reach Of Children

If swallowed, get medical help or contact a Poison control Center right away.

Directions

1. sunscrew the cap. For first-time use, remove the seal at the bottle mouth with scissors.

2. Clean and dry the affected area. Squeez the bottle gently to apply the liquid evenly, let It dry Into a film, and apply once more. 3.After use, seal the cap tightly to avoid air exposure and potential orystalization.

4. Apply once in the moming and once in the evening, with double application each time, For foot-related iseues, nighttime application is recommended for less friction and improved penetration.

5. Continue daily application for two weeks until the skin is fully restored.

Other information

store at room temperature In a sealed condition.

Inactive ingredients

Bassia Scoparia Fruit, Dictamnus Dasycarpus Root Bark, Gleditsia Sinensis Thorn, Typhonium Giganteum Stem

Questions

Call 1-646-798-1280